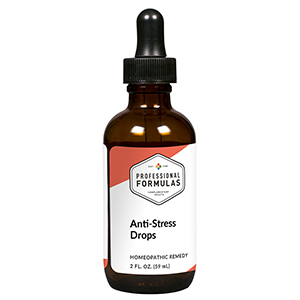 DRUG LABEL: Anti-Stress Drops
NDC: 63083-2009 | Form: LIQUID
Manufacturer: Professional Complementary Health Formulas
Category: homeopathic | Type: HUMAN OTC DRUG LABEL
Date: 20190815

ACTIVE INGREDIENTS: APIS MELLIFERA 2 [hp_X]/59 mL; ARTEMISIA ANNUA FLOWERING TOP 3 [hp_X]/59 mL; ROYAL JELLY 3 [hp_X]/59 mL; GELSEMIUM SEMPERVIRENS ROOT 3 [hp_X]/59 mL; CITRUS AURANTIUM FRUIT RIND 6 [hp_X]/59 mL; ORNITHOGALUM UMBELLATUM FLOWERING TOP 6 [hp_X]/59 mL; EPINEPHRINE 6 [hp_X]/59 mL; STRYCHNOS IGNATII SEED 6 [hp_X]/59 mL; NEUROTENSIN 16 [hp_X]/59 mL
INACTIVE INGREDIENTS: ALCOHOL; WATER

C9

ACTIVE INGREDIENTS

Apis mellifica 2X, 6X
Chamomilla 3X
Royal jelly 3X
Gelsemium sempervirens 3X, 6X
Citrus vulgaris 6X
Rescue remedy 6X
Adrenalinum 6X, 12X
Ignatia amara 6X, 12X, 30X
Neurotensin 16X, 30X

QUESTIONS

Professional Formulas

PO Box 2034 Lake Oswego, OR 97035

INDICATIONS

For temporary relief of anxiousness, irritability, fatigue, restlessness, muscle tension, or occasional headache associated with stressful situations.*

PURPOSE

*Claims based on traditional homeopathic practice, not accepted medical evidence. Not FDA evaluated.

WARNINGS

In case of overdose, get medical help or contact a poison control center right away.

Keep out of the reach of children.

PREGNANCY OR BREAST FEEDING

If pregnant or breastfeeding, ask a healthcare professional before use.

DIRECTIONS

Place drops under tongue 30 minutes before/after meals. Adults and children 12 years and over: Take 10 drops up to 3 times per day for up to 6 weeks. For immediate onset of symptoms, take 10 to 15 drops every 15 minutes up to 3 hours. For less severe symptoms, take 10-15 drops hourly up to 8 hours. Consult a physician for use in children under 12 years of age.

OTHER INFORMATION

Tamper resistant. If seal is broken, do not use. After opening, close container tightly and store at room temperature away from heat.

INACTIVE INGREDIENTS

20% ethanol, purified water.

LABEL

Est 1985

Professional Formulas

Complementary Health

Anti-Stress Drops

Homeopathic Remedy

2 FL. OZ. (59 mL)